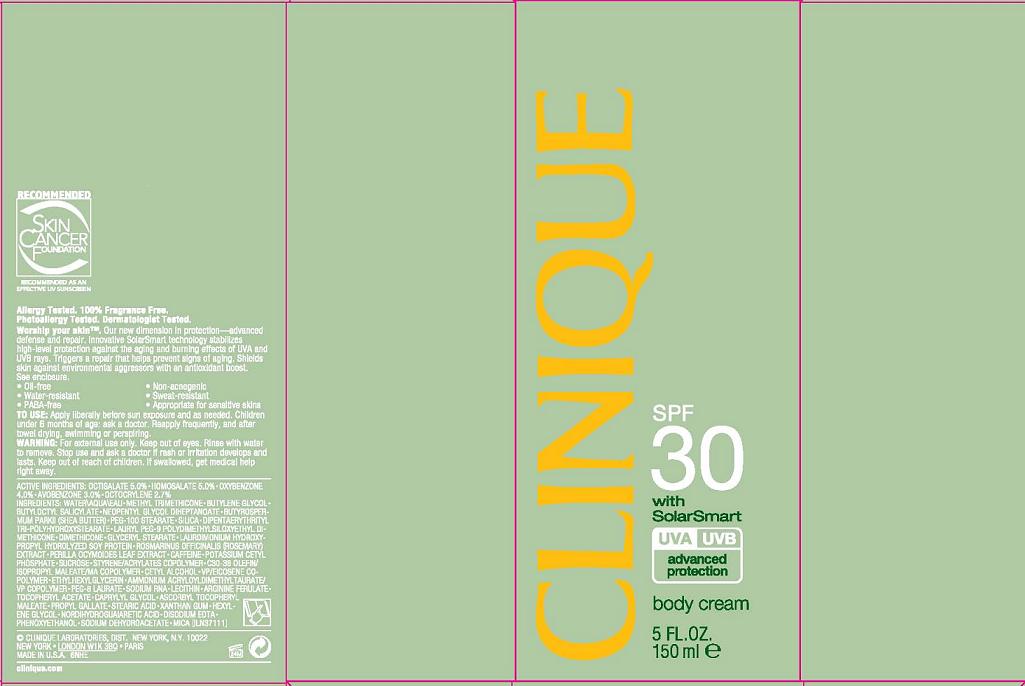 DRUG LABEL: CLINIQUE
NDC: 49527-736 | Form: CREAM
Manufacturer: CLINIQUE LABS INC
Category: otc | Type: HUMAN OTC DRUG LABEL
Date: 20110214

ACTIVE INGREDIENTS: OCTISALATE 5.0 mL/100 mL; HOMOSALATE 5.0 mL/100 mL; OXYBENZONE 4.0 mL/100 mL; AVOBENZONE 3.0 mL/100 mL; OCTOCRYLENE 2.7 mL/100 mL
INACTIVE INGREDIENTS: WATER; METHYL TRIMETHICONE; BUTYLENE GLYCOL; SHEA BUTTER; SILICON DIOXIDE; DIMETHICONE; GLYCERYL MONOSTEARATE; SUCROSE; LECITHIN, SOYBEAN; PHENOXYETHANOL; XANTHAN GUM; MICA

ACTIVE INGREDIENT

active ingredients: octisalate 5.00% [] homosalate 5.00% [] oxybenzone 4.00% [] avobenzone 3.00% [] octocrylene 2.70%

INACTIVE INGREDIENT

inactive ingredients: water [] methyl trimethicone [] butylene glycol [] butyloctyl salicylate [] neopentyl glycol diheptanoate [] butyrospermum parkii (shea butter) [] peg-100 stearate [] silica [] dipentaerythrityl tri-polyhydroxystearate [] lauryl peg-9 polydimethylsiloxyethyl dimethicone [] dimethicone [] glyceryl stearate [] laurdimonium hydroxypropyl hydrolyzed soy protein [] rosmarinus officinalis (rosemary) extract [] perilla ocymoides leaf extract [] caffeine [] potassium cetyl phosphate [] sucrose [] styrene/acrylates copolymer [] c30-38 olefin/isopropyl maleate/ma copolymer [] cetyl alcohol [] vp/eicosene copolymer [] ethylhexylglycerin [] ammonium acryloyldimethyltaurate/vp copolymer [] peg-8 laurate [] sodium rna [] lecithin [] arginine ferulate [] tocopheryl acetate [] caprylyl glycol [] ascorbyl tocopheryl maleate [] propyl gallate [] stearic acid [] xanthan gum [] hexylene glycol [] nordihydroguaiaretic acid [] disodium edta [] phenoxyethanol [] sodium dehydroacetate [] mica

WHEN USING

to use: apply liberally before sun exposure as needed. Reapply frequently, and after towel drying, swimming or perspiring

ASK DOCTOR/PHARMACIST

children under 6 months of age: ask a doctor

WARNINGS

warning: for external use only. keep out of eyes. rinse with water to remove.

stop use and ask a doctor if rash or irritation develops and lasts.

keep out of reach of children. if swallowed, get medical help right away.

PACKAGE LABEL

PRINCIPAL DISPLAY PANEL:

CLINIQUE

spf 30

WITH SOLAR SMART

UVA/UVB

ADVANCED PROTECTION

BODY CREAM

5 FL OZ/150 ML

clinique labs inc.

new york, ny 10022